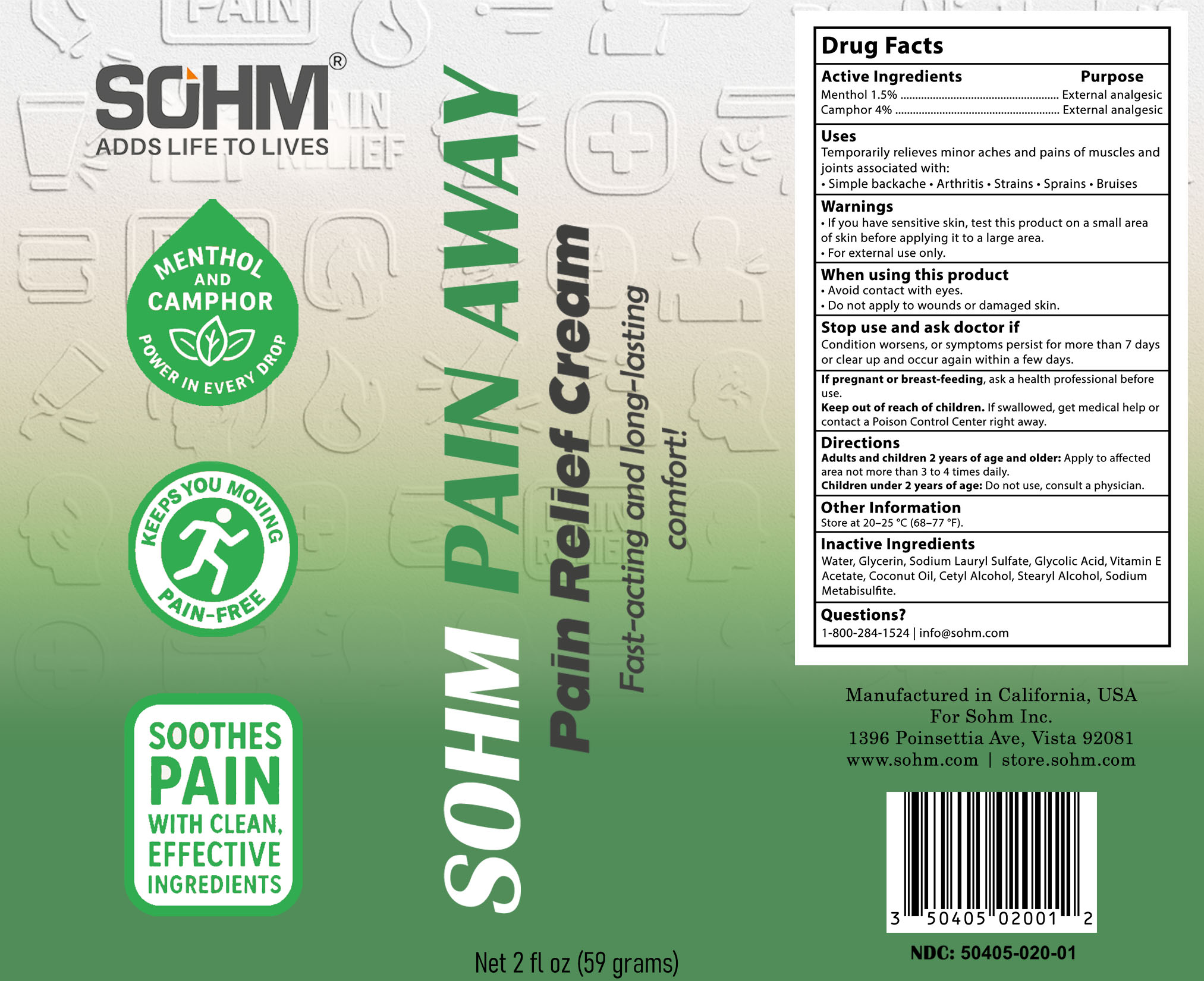 DRUG LABEL: Sohm Pain Away
NDC: 50405-020 | Form: CREAM
Manufacturer: SOHM, Inc
Category: otc | Type: HUMAN OTC DRUG LABEL
Date: 20251125

ACTIVE INGREDIENTS: MENTHOL 1.5 g/100 g; CAMPHOR (NATURAL) 4 g/100 g
INACTIVE INGREDIENTS: WATER; GLYCERIN; SODIUM LAURYL SULFATE; GLYCOLIC ACID; .ALPHA.-TOCOPHEROL ACETATE; COCONUT OIL; CETYL ALCOHOL; STEARYL ALCOHOL; SODIUM METABISULFITE

Sohm Pain Away Pain Relief Cream

Active Ingredients

Menthol 1.5%
Camphor 4%

Purpose

Menthol 1.5%......................................................External Analgesic
Camphor 4%....................................................... External Analgesic

Uses

Temporarily relieves minor aches and pains of muscles and joints associated with:
 simple backache
 arthritis
 strains
 bruises
 sprains

Warnings

- If you have senstive skin, test this product on a small area of skin before applying it to a large area
- For external use only.

When using this product
 Avoid contact with the eyes
 do not apply to wounds or damaged skin

Stop use and ask a doctor if
 condition worsens, or if symptoms persist for more than 7 days or clear up and occur again within a few days

PREGNANCY OR BREAST FEEDING

If pregnant or breast-feeding, ask a health professional before use.

Keep out of reach of children. If swallowed, get medical help or contact a Poison Control Center right away.

Directions

Adults and children 2 years of age and older: Apply to affected area not more than 3 to 4 times daily.
Children under 2 years of age: Do not use, consult a physician

Other information

store at 20–25ºC (68–77ºF)

Inactive Ingredients

Water, Glycerin, Sodium Lauryl Sulfate, Glycolic acid, Vitamin E Acetate, Coconut Oil, Cetyl Alcohol, Stearyl Alcohol, sodium metabisulfite.

Questions?

1-800-284-1524 or info@sohm.com